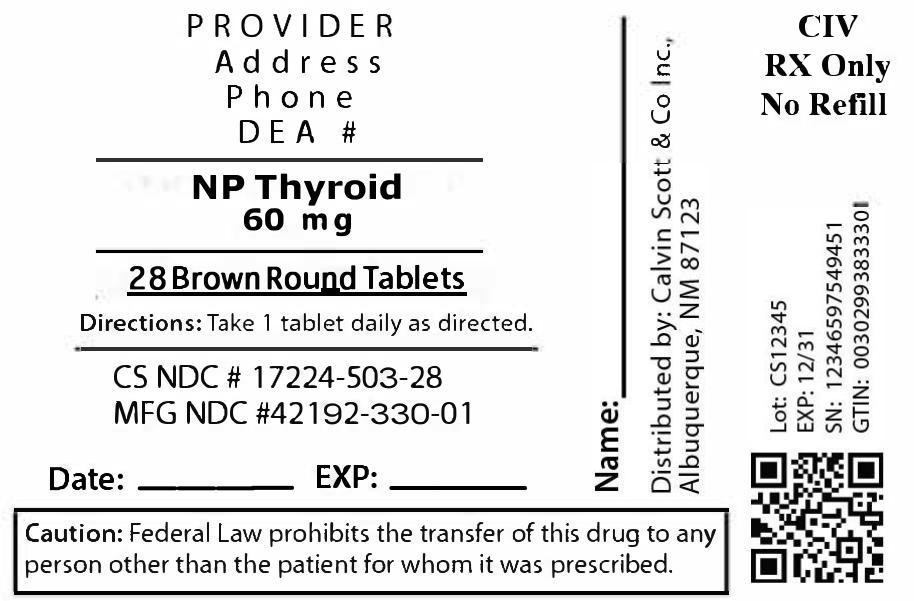 DRUG LABEL: NP Thyroid
NDC: 17224-503 | Form: TABLET
Manufacturer: Calvin Scott & Co Inc.
Category: otc | Type: HUMAN OTC DRUG LABEL
Date: 20250810

ACTIVE INGREDIENTS: LEVOTHYROXINE 38 ug/1 1; LIOTHYRONINE 9 ug/1 1
INACTIVE INGREDIENTS: DEXTROSE MONOHYDRATE; MINERAL OIL; CALCIUM STEARATE; MALTODEXTRIN

DOSAGE AND ADMINISTRATION

Take 1 tablet daily on an empty stomach or as directed.

WARNINGS

Do not exceed recommended dose. Keep out of reach of children.

INACTIVE INGREDIENT

Calcium stearate, dextrose, maltodextrin, mineral oil, modified wheat starch

INDICATIONS AND USAGE

Used as a thyroid hormone replacement for hypothyroidism.

PURPOSE

Thyroid hormone replacement

ACTIVE INGREDIENT

Thyroid 60 mg

Keep out of reach of children. In case of accidental overdose, contact a doctor or Poison Control Center immediately.

NDC 17224-503-28

Package label for NP Thyroid 60 mg tablets (28 tablets per bottle). Contains product name, dosage strength, NDC 17224-503-28, manufacturer/repacker name, and usage instructions as printed on the label.